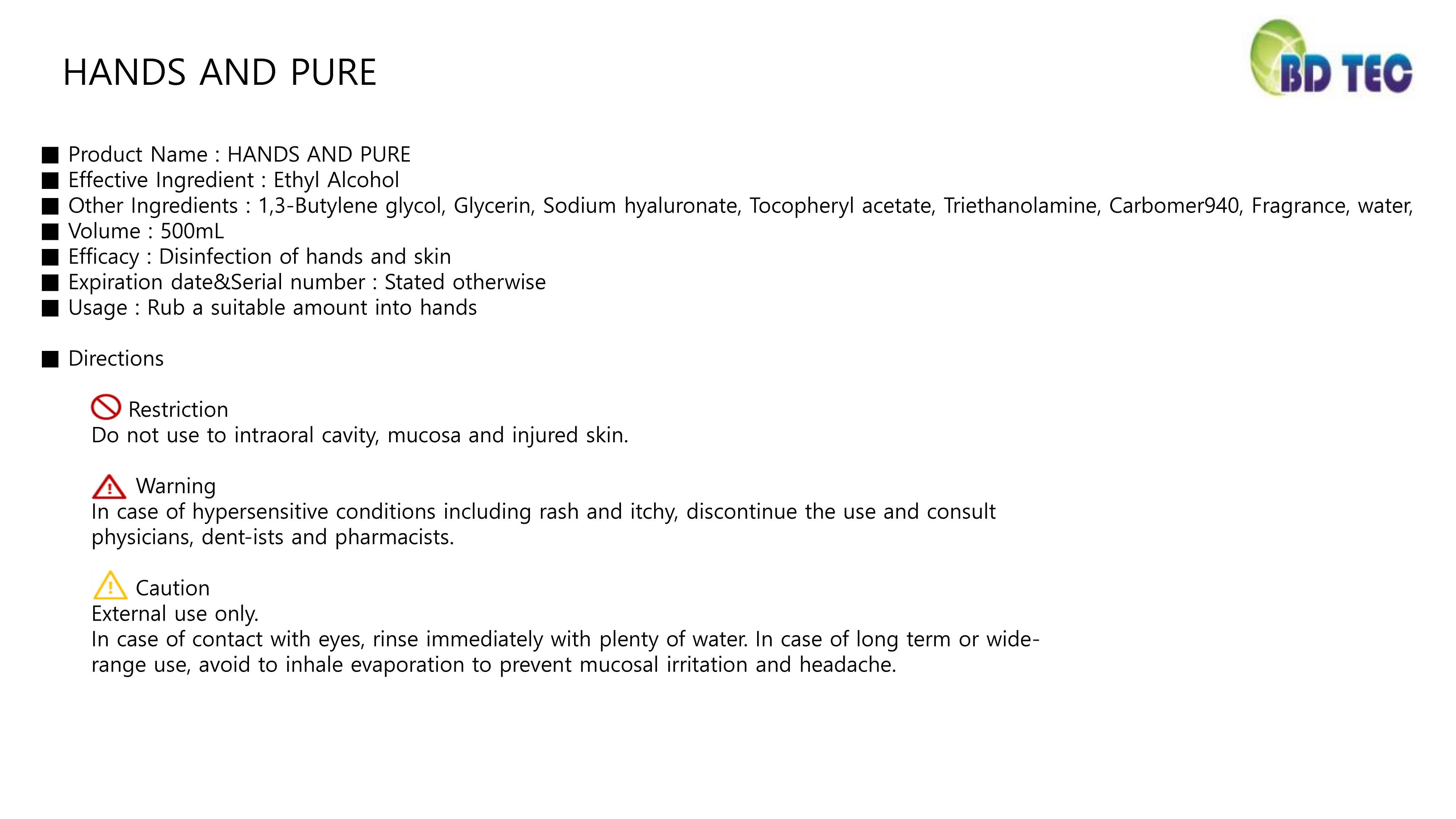 DRUG LABEL: Soom Mouthwash
NDC: 73927-0005 | Form: LIQUID
Manufacturer: BD TECHNOLOGY CO., LTD
Category: otc | Type: HUMAN OTC DRUG LABEL
Date: 20200610

ACTIVE INGREDIENTS: SODIUM FLUORIDE 0.02 g/100 mL
INACTIVE INGREDIENTS: GLYCERIN; ALLANTOIN; WATER; ERYTHRITOL

Drug Facts

ACTIVE INGREDIENT

sodium fluoride

INACTIVE INGREDIENT

Water
Sodium Fluoride
Allantoin
Erythritol
xylitol
Sodium benzoate
Glycerin
Propylene Glycol
PEG-40 Hydrogenated Castor Oil
L-Menthol
zinc gluconate
sodium citrate
Fragrance

PURPOSE

prevention of gingvitis, periodontitis, cavity, periodontal disease gum disease

KEEP OUT OF REACH OF THE CHILDREN

INDICATIONS AND USAGE

spit out the appropriate amount (120~15ml) for about 30 seconds after mouthing, and then brush the tooth bybrushing

WARNINGS

For oral use only.

When using this product keep out of eyes. If contact with eyes occurs, rinse promptly and thoroughly with water.

Stop use and ask a doctor if significant irritation or sensitization develops.

DOSAGE AND ADMINISTRATION

for oral use only